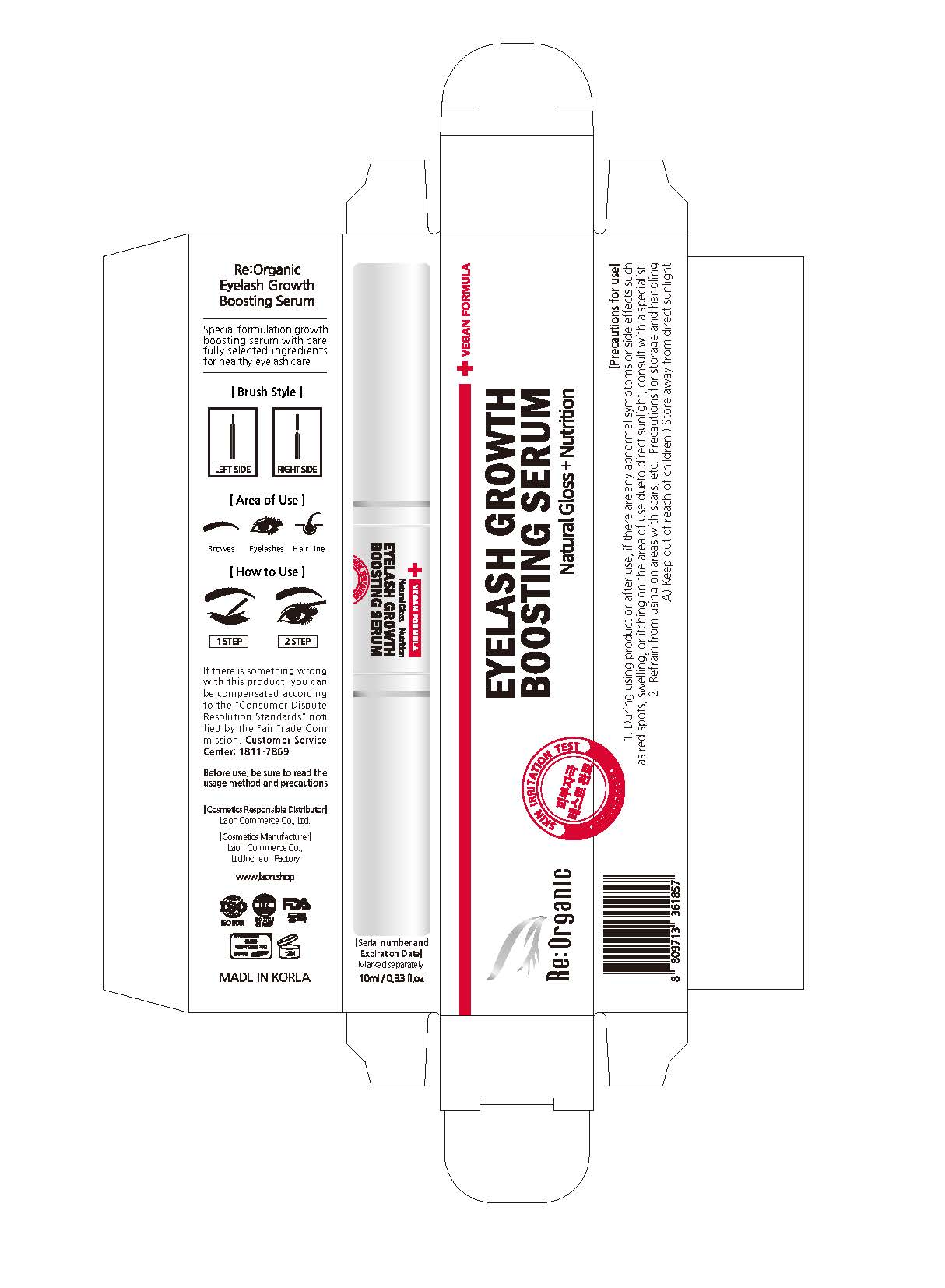 DRUG LABEL: ReOrganic Eyelash Growth Boosting Serum
NDC: 82083-0024 | Form: LIQUID
Manufacturer: LAON COMMERCE co ltd
Category: otc | Type: HUMAN OTC DRUG LABEL
Date: 20230912

ACTIVE INGREDIENTS: PANTHENOL 0.501 g/100 mL
INACTIVE INGREDIENTS: BIOTIN; GLYCERIN; WATER; HYALURONATE SODIUM

ACTIVE INGREDIENT

Panthenol

INACTIVE INGREDIENT

Water
Butylene Glycol
Pentylene Glycol
1,2-Hexanediol
Sodium Hyaluronate
Glycerin
Ethylhexylglycerin
PEG-40 Hydrogenated Castor Oil
PPG-26-Buteth-26
Hydrogenated Lecithin
Caprylyl Glycol
Polyglyceryl-10 Stearate
Myristoyl Pentapeptide-17
Sodium Ascorbyl Phosphate
Tocopheryl Acetate
Glyceryl Linolenate
Glyceryl Arachidonate
Retinyl Palmitate
Biotin
Thiamine HCl
Folic Acid
Pyridoxine
Cyanocobalamin

PURPOSE

skin protect

KEEP OUT OF REACH OF THE CHILDREN

INDICATIONS AND USAGE

1 step. Apply a small amount of the serum to the roots of the eyelashes and leave them to be absorbed.

2 step. Apply the serum evenly on the tips of the eyelashes and let it absorb.

WARNINGS

1. During using product or after use, if there are any abnormal symptoms or side effects such as red spots, swelling or itching in the area of use due to direct sunlight, consult with a specialist.

2. Refrain from using on areas with scars, etc.

3. Precautions for storage and handling

A) Keep out of reach of children

B) Store away from direct sunlight

DOSAGE AND ADMINISTRATION

topical use only